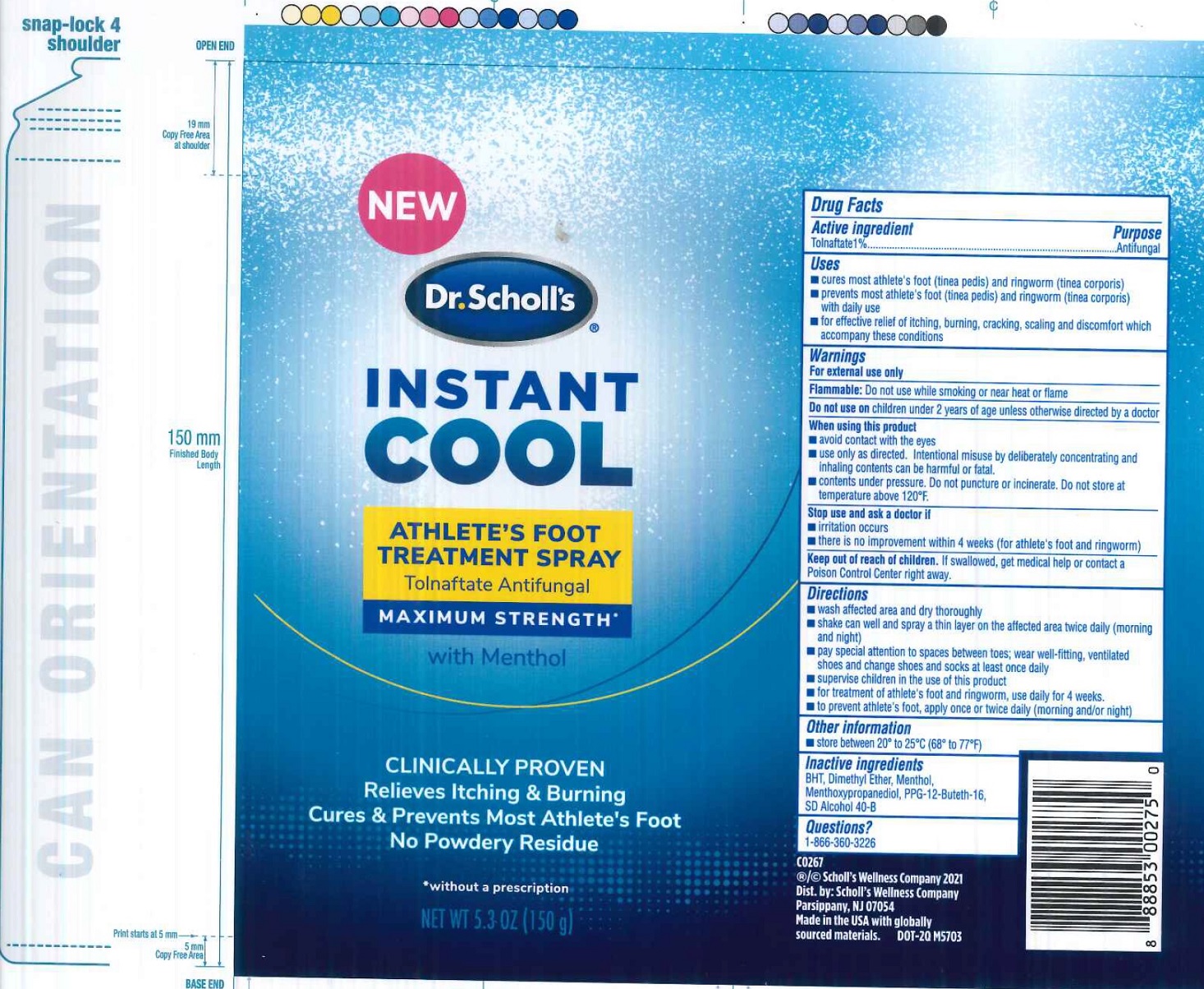 DRUG LABEL: Dr. Scholls Instant Cool Athletes foot treatment with Menthol
NDC: 73469-0691 | Form: SPRAY
Manufacturer: Scholl's Wellness Company
Category: otc | Type: HUMAN OTC DRUG LABEL
Date: 20231221

ACTIVE INGREDIENTS: TOLNAFTATE 10 mg/1 g
INACTIVE INGREDIENTS: BUTYLATED HYDROXYTOLUENE; DIMETHYL ETHER; MENTHOL; 3-((L-MENTHYL)OXY)PROPANE-1,2-DIOL; PPG-12-BUTETH-16

Dr. Scholl's Instant Cool Athlete's foot treatment Spray with Menthol

Active ingredient

Tolnaftate 1%

Purpose

Antifungal

Uses

- cures most athlete's foot (tinea pedis) and ringworm (tinea corporis)
- prevents most athlete's foot (tinea pedis) and ringworm (tinea corporis) with daily use
- for effective relief of itching, burning, cracking, scaling and discomfort which accompany these conditions

Warnings

For external use only

Do not use while smoking or near heat or flame Flammable:

Do not use on

children under 2 years of age unless otherwise directed by a doctor

When using this product

- avoid contact with the eyes
- use only as directed. Interntional misuse by deliberately concentrating and inhaling contents can be harmful or fatal.
- contents under pressure. Do not puncture or incinerate. Do not store at temperature above 120°F.

Stop use and ask a doctor if

- irritation occurs
- there is no improvement within 4 weeks (for athlete's foot and ringworm)

Keep out of reach of children.

If swallowed, get medical help or contact a Poison Control Center right away.

Directions

- wash affected area and dry thoroughly
- shake can well and spray a thin layer on the affected area twice daily (morning and night)
- pay special attention to spaces between toes; wear well-fitting, ventilated shoes and change shoes and socks at least once daily
- supervise children in the use of this product
- for treatment of athlete's foot and ringworm, use daily for 4 weeks.
- to prevent athlete's foot, apply once a twice daily (morning and/or night)

Other information

- store between 20° to 25°C (68° to 77°F)

Inactive ingredients

BHT, Dimethyl Ether, Menthol, Menthoxypropanediol, PPG-12-Buteth-16, SD Alcohol 40-B

Questions?

1-866-360-3226